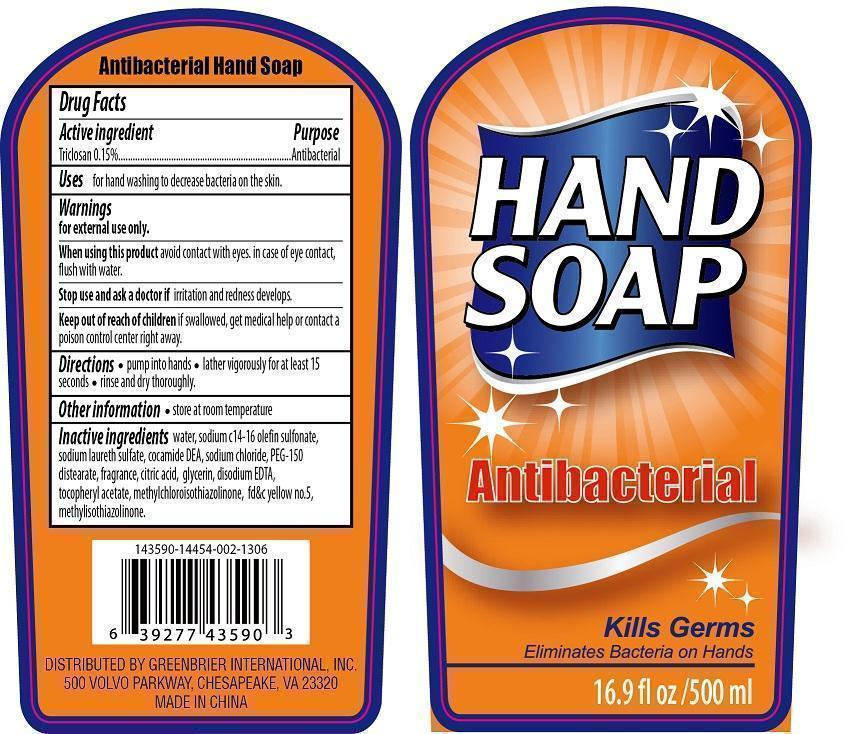 DRUG LABEL: Hand Cleanse
NDC: 58503-009 | Form: GEL
Manufacturer: China Ningbo Shangge Cosmetic Technology Corp.
Category: otc | Type: HUMAN OTC DRUG LABEL
Date: 20221117

ACTIVE INGREDIENTS: TRICLOSAN 7.5 mg/500 mg
INACTIVE INGREDIENTS: WATER; SODIUM C14-16 OLEFIN SULFONATE; SODIUM LAURETH SULFATE; COCO DIETHANOLAMIDE; SODIUM CHLORIDE; PEG-150 DISTEARATE; CITRIC ACID MONOHYDRATE; GLYCERIN; EDETATE DISODIUM; .ALPHA.-TOCOPHEROL ACETATE; METHYLCHLOROISOTHIAZOLINONE; FD&C YELLOW NO. 5; METHYLISOTHIAZOLINONE

Hand Cleanse

Active Ingredient Purpose

Triclosan 0.15%..................................Antibacterial

Uses

forthe temporary relief of minor aches and pains of muscles and joints.

Keep out of reach of children. In case of accidental ingestion, seek professional assistance or contact a Poison Control Center immediately.

Other information

- store at 20oC to 25oC (68o to 77oF)

Warnings

For external use only. Avoid contact with eyes.

Ask a doctor before use if you have cough associated with

- smoking
- excessive phlegm
- asthma
- emphysema
- persistent or chronic cough

When using this product do not

- heat
- microwafe
- add to hot water or any container where healing water may cause splattering and result in burns
- use in eyes or directly on mucous membranes
- take by mouth or place in nostrils
- apply to wounds or damaged skin
- bandage skin

Consult a doctor and discontinue use if condition worsesn, persists for more than 1 week or tends to recur.

Directions

- see important warnings under "When using this product"
- adults & children 2 years of age & older: apply to the affected area not more than 3 to 4 times daily.
- children under 2 years of age: consult a physician.

Inactive Ingredients

camphor, carbomer, ethyl alcohol, fd&c blue no.1, isopropyl alcohol, methylchloroisothiazolinone, methylisothiazolinone, sodium hydroxide, water.